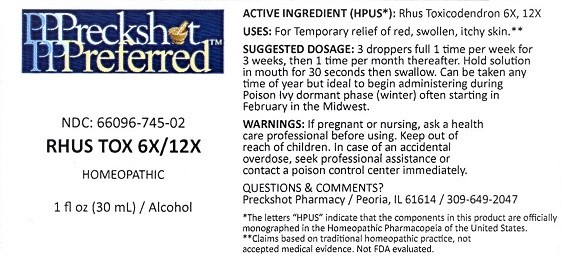 DRUG LABEL: RHUS TOX 6X/12X
NDC: 66096-745 | Form: LIQUID
Manufacturer: OHM PHARMA INC.
Category: homeopathic | Type: HUMAN OTC DRUG LABEL
Date: 20181029

ACTIVE INGREDIENTS: TOXICODENDRON PUBESCENS LEAF 6 [hp_X]/30 mL
INACTIVE INGREDIENTS: ALCOHOL

RHUS TOX 6x/12x

ACTIVE INGREDIENT (HPUS*):

Rhus Toxicodendron 6X/12X

*The letters "HPUS" indicate that the components in this product are officially monographed in the Homeopathic Pharmacopeia of the United States.

**Claims based on traditional homeopathic practice, not accepted medical evidence. Not FDA evaluated.

INDICATIONS AND USAGE

USES: For Temporary relief of red, swollen, itchy skin.**

SUGGESTED DOSAGE:

3 droppers full 1 time per week for 3 weeks, then 1 time per month thereafter. Hold solution in mouth for 30 seconds then swallow.

Can be taken any time of year but ideal to begin administering during Poision Ivy dormant phase (winter) often starting in February

in the Midwest.

WARNINGS:

If pregnant or nursing, ask a health care professional before using.

Keep out of reach of children. In case of an accidental overdose, seek professional assistance or contact a poison control center immediately.

Keep out of reach of children.

INACTIVE INGREDIENT

Alcohol

QUESTIONS & COMMENTS?

Preckshot Pharmacy / Peoria, IL 61614 / 309-649-2047

PACKAGE LABEL

Preckshot Preferred ™

NDC: 66096-745-02

RHUS TOX 6X/12X

HOMEOPATHIC

1 fl oz (30 mL) / Alcohol

PURPOSE

For Temporary relief of red, swollen, itchy skin.**